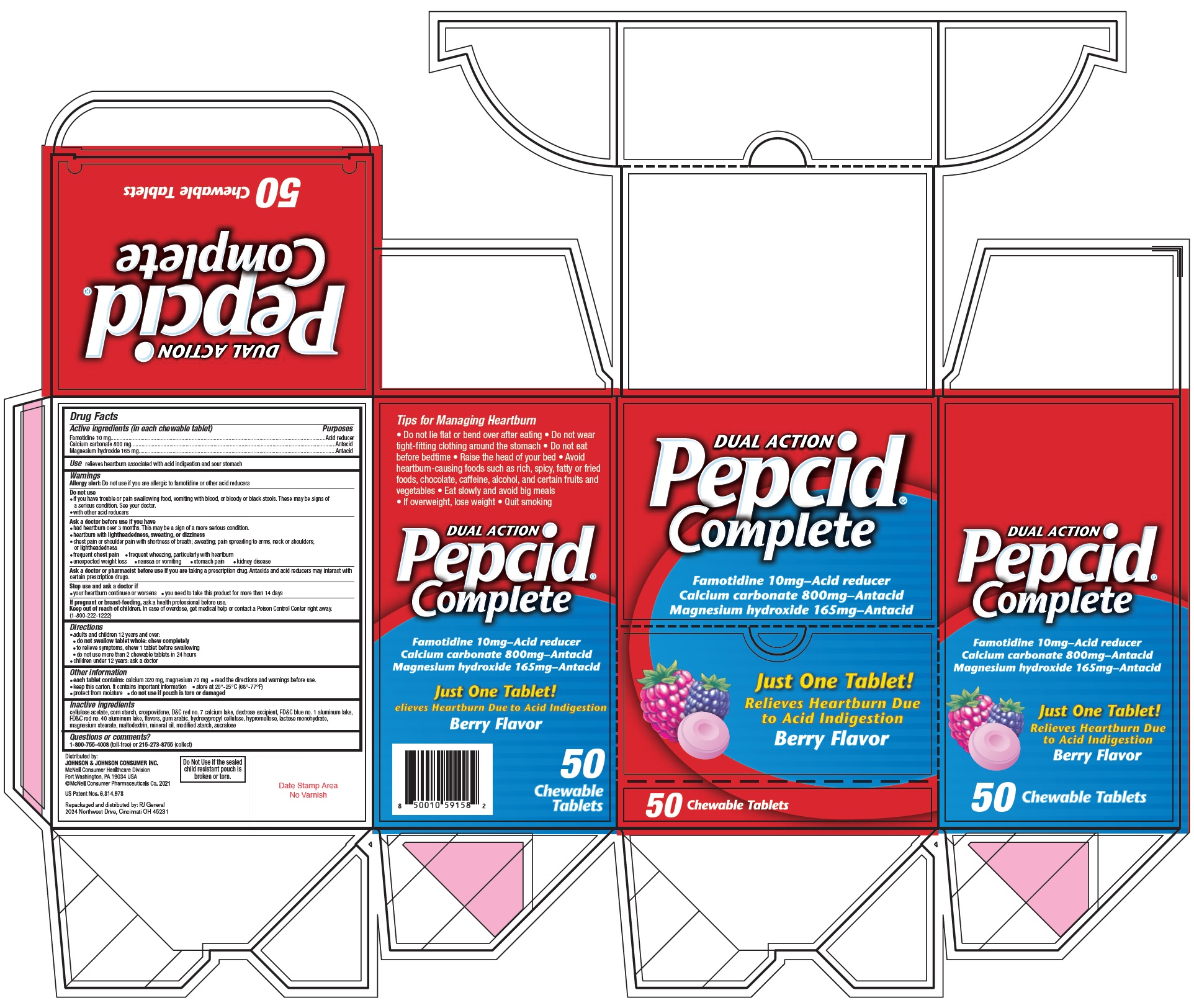 DRUG LABEL: Pepcid Complete
NDC: 70264-034 | Form: TABLET, CHEWABLE
Manufacturer: R J General Corporation
Category: otc | Type: HUMAN OTC DRUG LABEL
Date: 20251117

ACTIVE INGREDIENTS: FAMOTIDINE 10 mg/1 1; CALCIUM CARBONATE 800 mg/1 1; MAGNESIUM HYDROXIDE 165 mg/1 1
INACTIVE INGREDIENTS: CELLULOSE ACETATE; STARCH, CORN; CROSPOVIDONE; D&C RED NO. 7; DEXTROSE, UNSPECIFIED FORM; FD&C RED NO. 3; ACACIA; HYDROXYPROPYL CELLULOSE, UNSPECIFIED; HYPROMELLOSE, UNSPECIFIED; LACTOSE MONOHYDRATE; MAGNESIUM STEARATE; MALTODEXTRIN; MINERAL OIL; SUCRALOSE

Pepcid Complete

Drug Facts

ACTIVE INGREDIENT

PURPOSE

Active ingredients (in each chewable tablet) | Purposes
Famotidine 10 mg | Acid reducer
Calcium carbonate 800 mg | Antacid
Magnesium hydroxide 165 mg | Antacid

Use

relieves heartburn associated with acid indigestion and sour stomach

Warnings

Allergy alert

Do not use if you are allergic to famotidine or other acid reducers

Do not use

- if you have trouble or pain swallowing food, vomiting with blood, or bloody or black stools. These may be signs of a serious condition. See your doctor.
- with other acid reducers

Ask a doctor before use if you have

- had heartburn over 3 months. This may be a sign of a more serious condition.
- heartburn with lightheadedness, sweating, or dizziness
- chest pain or shoulder pain with shortness of breath; sweating; pain spreading to arms, neck or shoulders; or lightheadedness
- frequent chest pain
- frequent wheezing, particularly with heartburn
- unexplained weight loss
- nausea or vomiting
- stomach pain
- kidney disease

Ask a doctor or pharmacist before use if you aretaking a prescription drug. Antacids and acid reducers may interact with certain prescription drugs.

Stop use and ask a doctor if

- your heartburn continues or worsens
- you need to take this product for more than 14 days

PREGNANCY OR BREAST FEEDING

If pregnant or breast-feeding,ask a health professional before use.

Keep out of reach of children.In case of overdose, get medical help or contact a Poison Control Center right away. (1-800-222-1222)

Directions

- adults and children 12 years and over:
  - do not swallow tablet whole: chew completely
  - to relieve symptoms, chew1 tablet before swallowing
  - do not use more than 2 chewable tablets in 24 hours
- children under 12 years: ask a doctor

Other information

- each tablet contains:calcium 320 mg, magnesium 70 mg
- read the directions and warnings before use
- keep this carton. It contains important information
- store at 20°-25°C (68°-77°F)
- protect from moisture
- do not use if pouch is torn or damaged

Inactive ingredients

cellulose acetate, corn starch, crospovidone, D&C red no. 7 calcium lake, dextrose excipient, FD&C blue no. 1 aluminum lake, FD&C red no. 40 aluminum lake, flavors, gum arabic, hydroxypropyl cellulose, hypromellose, lactose monohydrate, magnesium stearate, maltodextrin, mineral oil, modified starch, sucralose

Questions or comments?

call 1-800-755-4008(toll-free) or 215-273-8755(collect)

Distributed by:

JOHNSON & JOHNSON CONSUMER INC.

McNeil Consumer Healthcare Division

For Washington, PA 19034 USA

Repackaged and distributed by: RJ General

2024 Northwest Drive, Cincinnati OH 45231

Do Not Use if the sealed child resistant pouch is broken or torn

PRINCIPAL DISPLAY PANEL

NDC 70264-034-01

DUAL ACTION
Pepcid®
Complete

Famotidine 10 mg–Acid reducer
Calcium carbonate 800 mg–Antacid
Magnesium hydroxide 165 mg–Antacid

Just One Tablet!
Relieves Heartburn Due to Acid Indigestion
Berry Flavor

50 Chewable Tablets